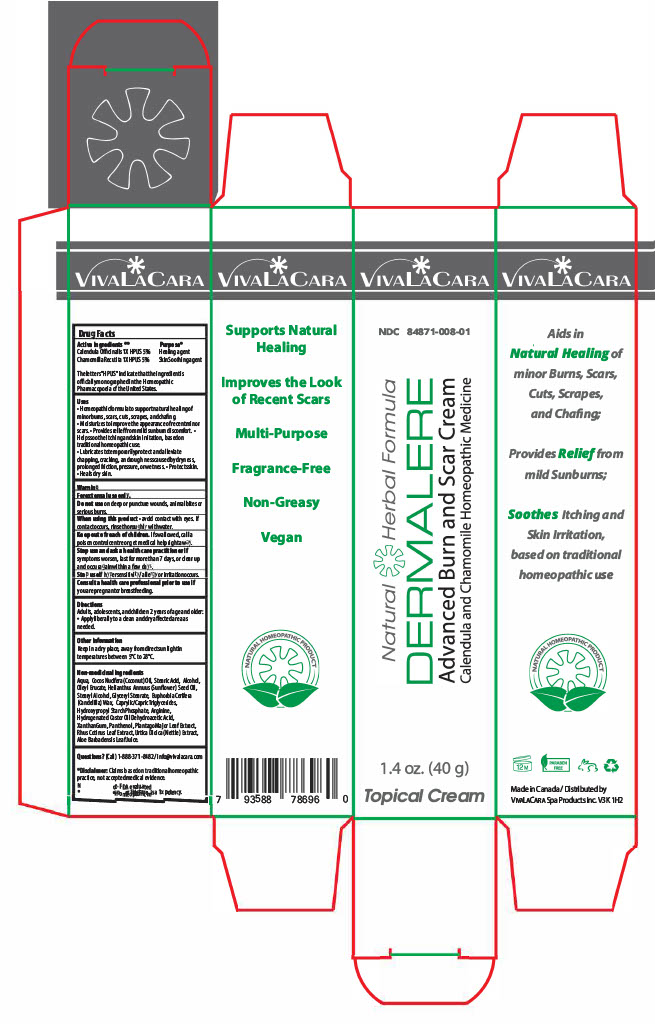 DRUG LABEL: VivaLaCara Dermalere Advanced Burn and Scar Cream
NDC: 84871-008 | Form: CREAM
Manufacturer: VivaLaCara Spa Products Inc.
Category: homeopathic | Type: HUMAN OTC DRUG LABEL
Date: 20250119

ACTIVE INGREDIENTS: CALENDULA OFFICINALIS FLOWER 5 g/100 g; CHAMOMILE 5 g/100 g
INACTIVE INGREDIENTS: AQUA; COCOS NUCIFERA (COCONUT) OIL; URTICA DIOICA LEAF; STEARYL ALCOHOL; GLYCERYL MONOSTEARATE; CAPRYLIC/CAPRIC TRIGLYCERIDE; COTINUS COGGYGRIA LEAF; OLEYL ERUCATE; HELIANTHUS ANNUUS (SUNFLOWER) SEED OIL; DEXPANTHENOL; ALOE BARBADENSIS LEAF JUICE; EUPHORBIA CERIFERA (CANDELILLA) WAX; STEARIC ACID; ALCOHOL; STARCH, CORN; HYDROGENATED CASTOR OIL; DEHYDROACETIC ACID; XANTHAN GUM; PLANTAGO MAJOR LEAF; ARGININE

Active Ingredient Section

Calendula Officinalis 1X HPUS 5% Purpose Healing agent

Chamomilla Recutita 1X HPUS 5% Purpose Skin Soothing agent

The letters "HPUS" indicate that the ingredient is officially monographed in the Homeopathic Pharmacopoeia of the United States.

Purpose

Healing, Skin Soothing

Uses

•Homeopathic formula to support natural healing of minor burns, scars, cuts, scrapes, and chafing.

• Moisturizes to improve the appearance of recent minor scars.

• Provides relief from mild sunburn discomfort.

• Helps soothe itching and skin irritation, based on traditional homeopathic use.

• Lubricates to temporarily protect and alleviate chapping, cracking, and roughness caused by dryness, prolonged friction, pressure, or wetness.

• Protects skin.

• Heals dry skin.

Warning

For external use only.

Do not use on deep or puncture wounds, animal bites or serious burns.

When using

When using this product • avoid contact with eyes. If contact occurs, rinse thoroughly with water.

Keep out of reach of children. If swallowed, call a poison control centre or get medical help right away.

Stop use

Stop use and ask a health care practitioner if symptoms worsen, last for more than 7 days, or clear up and occur again within a few days.

Stop use if hypersensitivity/ allergy or irritation occurs.

Pregnancy or breast feeding

Consult a health care professional prior to use if you are pregnant or breastfeeding.

Other information

Keep in a dry place, away from direct sunlight in temperatures between 5°C to 28°C.

Mon-medicinal ingredients

Aqua, Cocos Nucifera (Coconut) Oil, Stearic Acid, Alcohol, Oleyl Erucate, Helianthus Annuus (Sunflower) Seed Oil, Stearyl Alcohol, Glyceryl Stearate, Euphorbia Cerifera (Candelilla) Wax, Caprylic/Capric Triglycerides, Hydroxypropyl Starch Phosphate, Arginine, Hydrogenated Castor Oil Dehydroacetic Acid, Xanthan Gum, Panthenol, Plantago Major Leaf Extract, Rhus Cotinus Leaf Extract, Urtica Dioica (Nettle) Extract, Aloe Barbadensis Leaf Juice.

Questions and Disclaimer

Questions? (Call) 1-888-371-8482 / info@vivalacara.com

*Disclaimer: Claims based on traditional homeopathic practice, not accepted medical evidence. Not FDA evaluated.

**Homeopathic mother tincture is a 1x potency.

Directions

Adults, adolescents, and children 2 years of age and older: •Apply liberally to a clean and dry affected area as needed.

PACKAGE LABEL

NDC 84871-008-01

Natural Herbal Formula

DERMALERE

Advanced Burn and Scar Skin Cream

Calendula and Chamomile Homeopathic Medicine

40 g